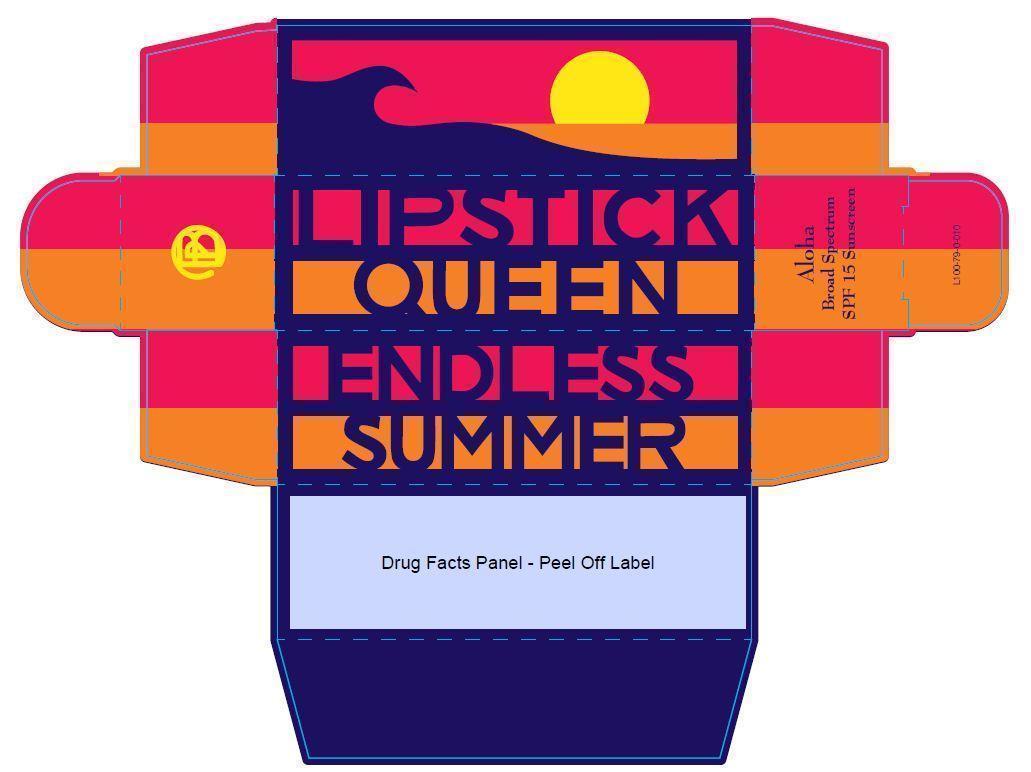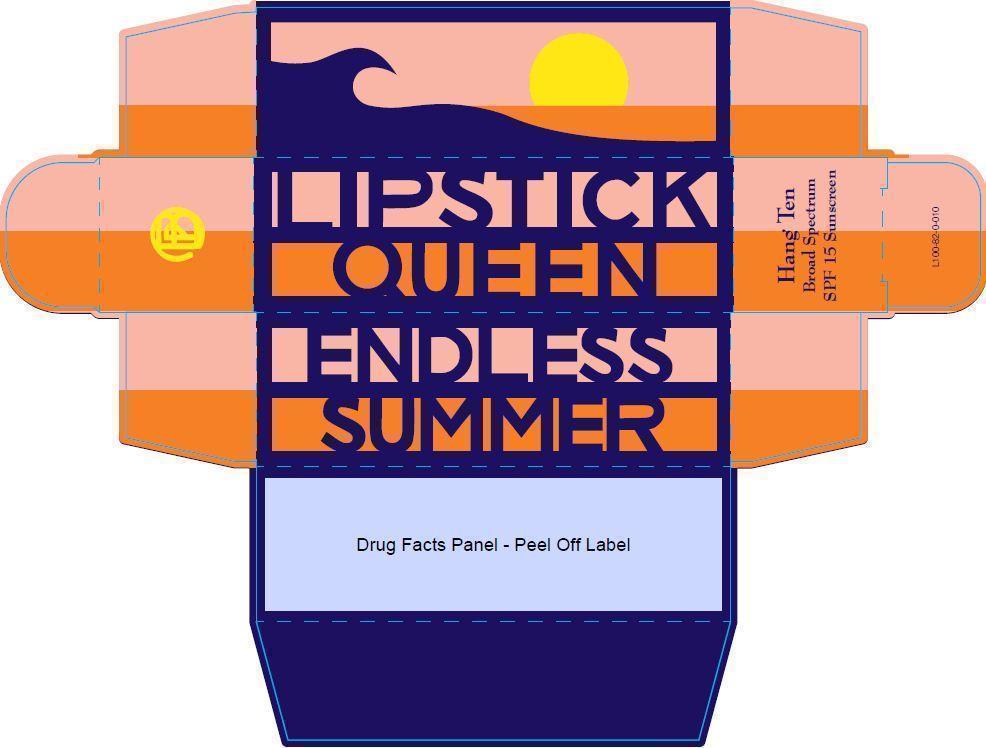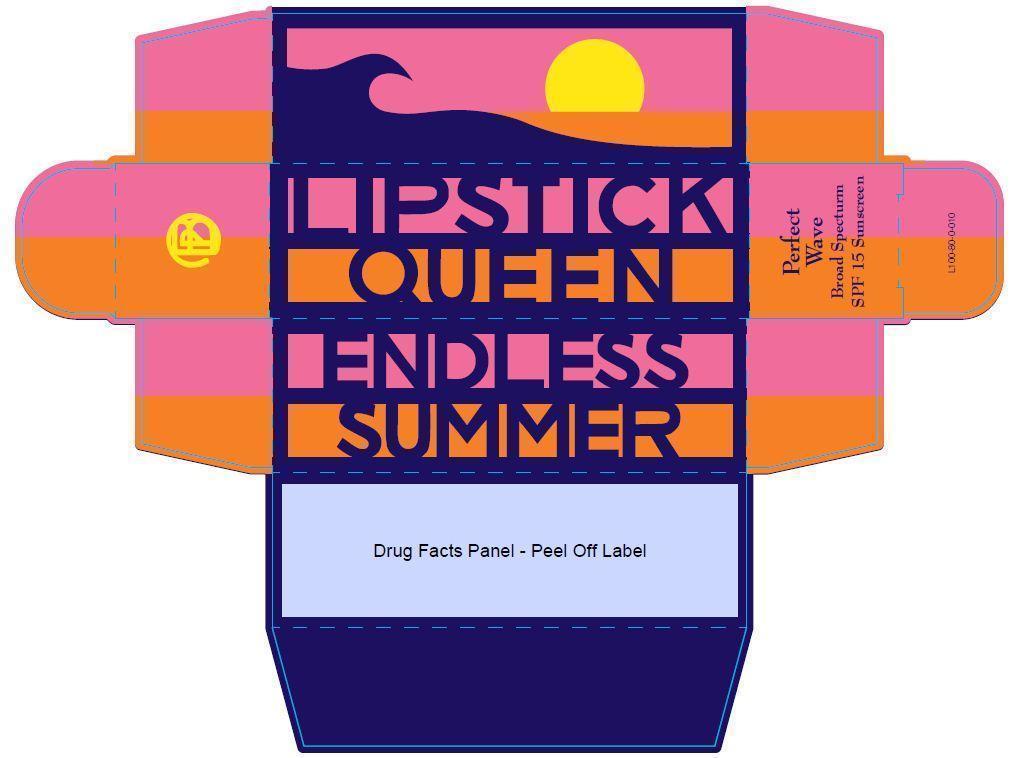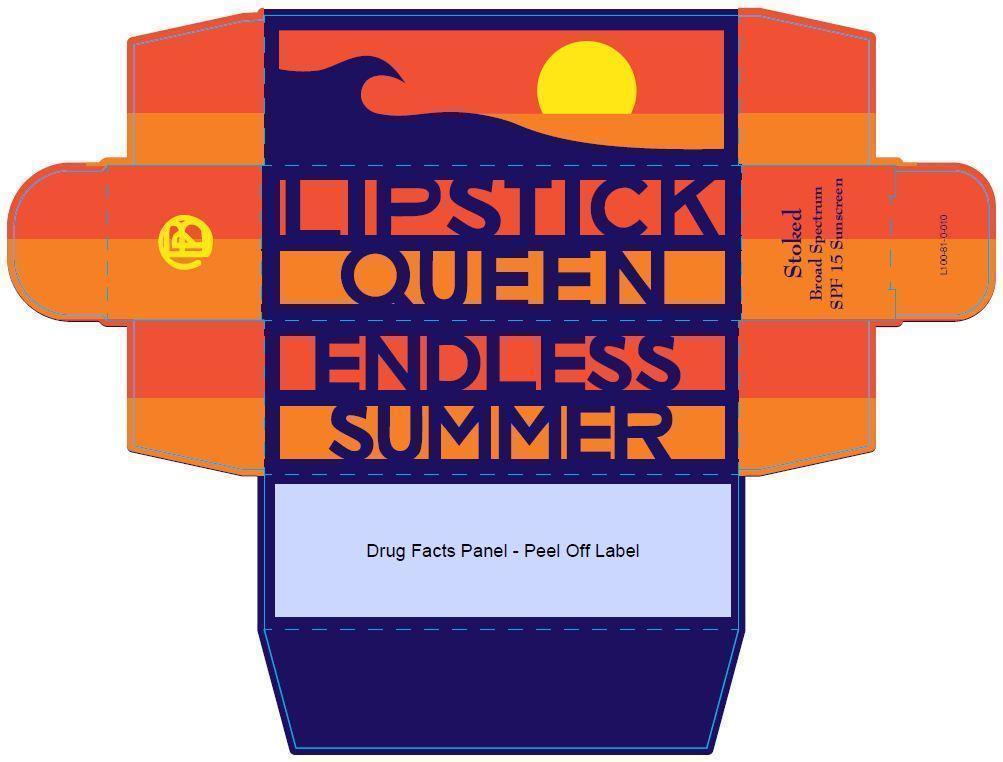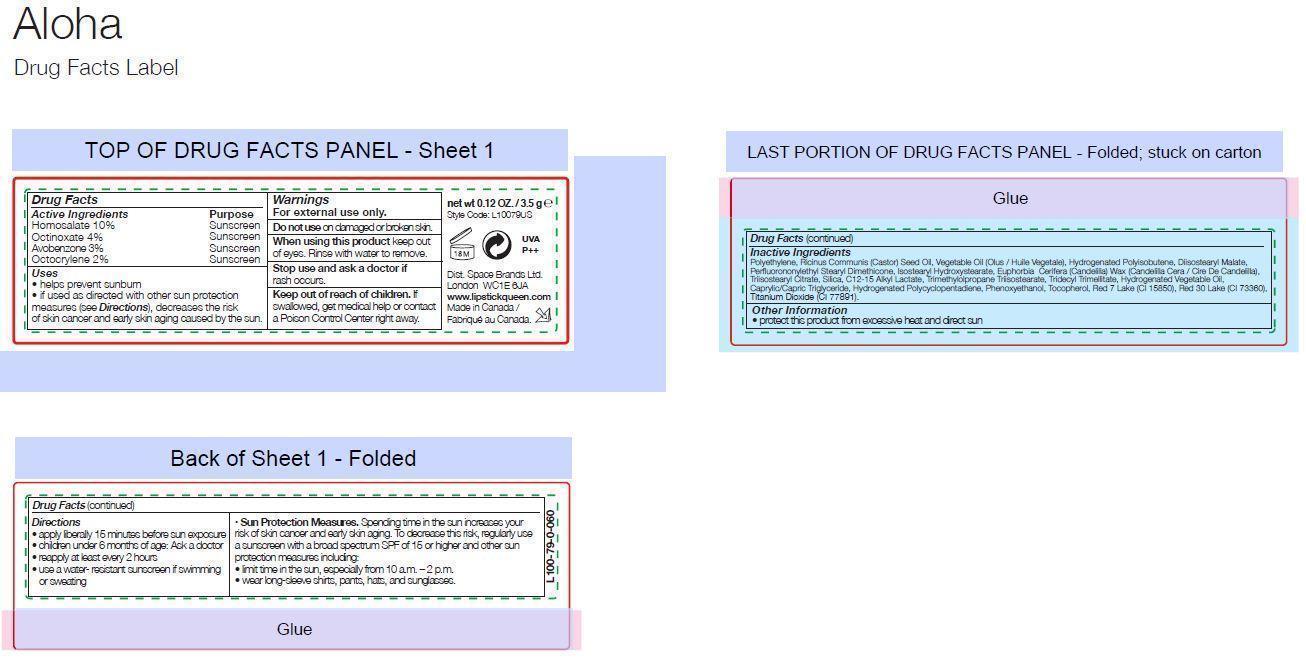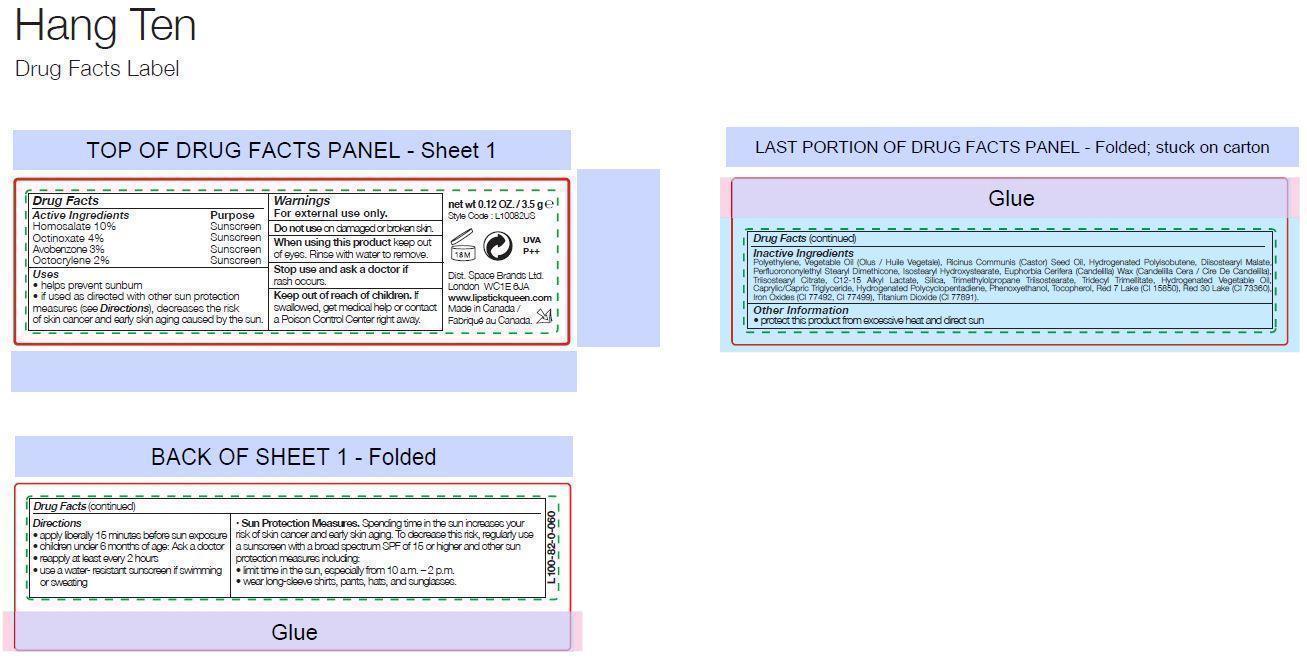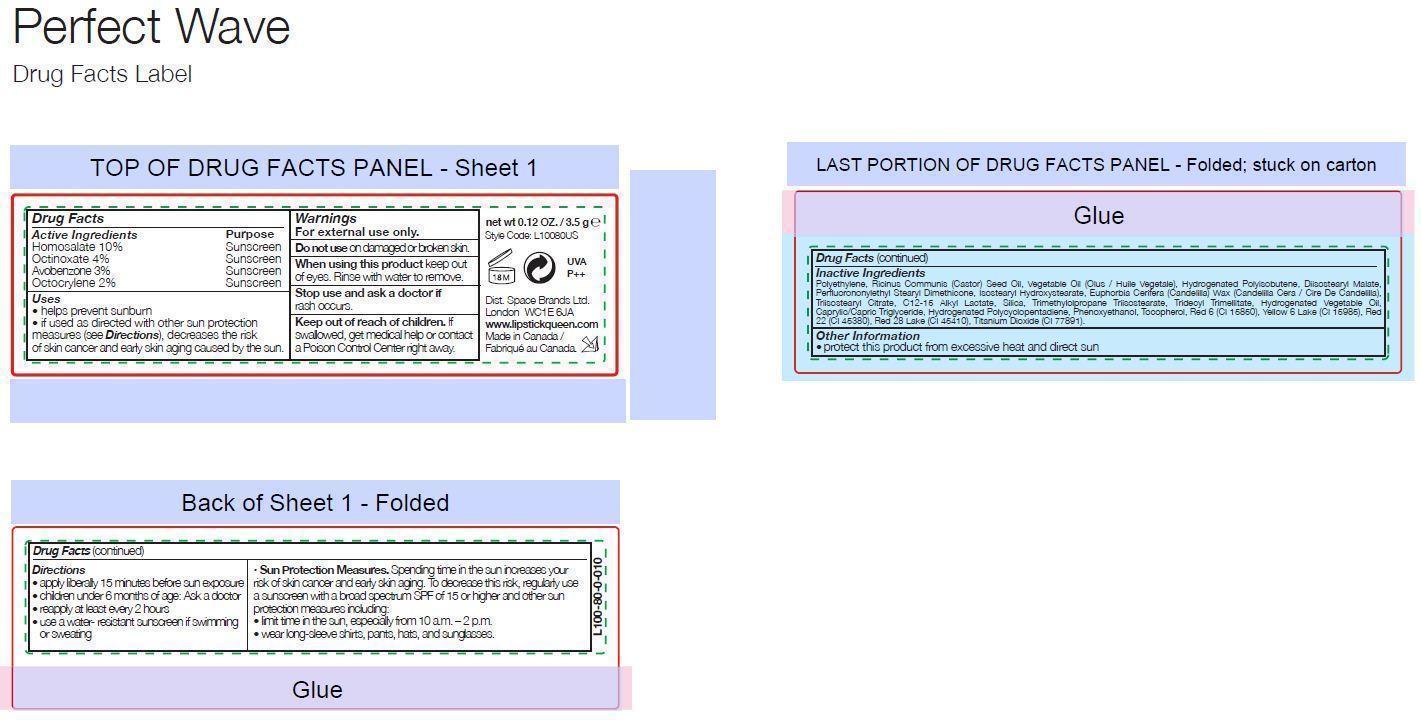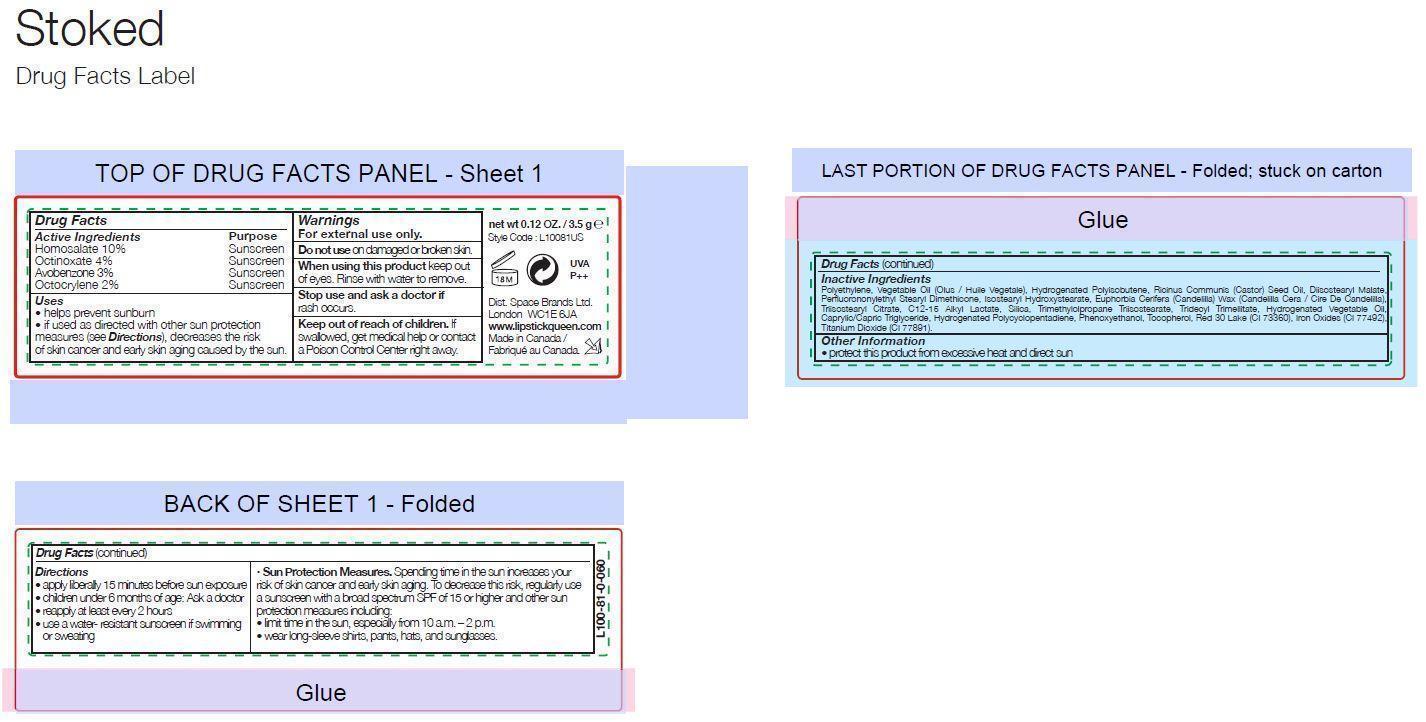 DRUG LABEL: LIPSTICK QUEEN ENDLESS SUMMER Broad Spectrum SPF 15 Sunscreen
NDC: 61601-0079 | Form: LIPSTICK
Manufacturer: Space Brands Limited
Category: otc | Type: HUMAN OTC DRUG LABEL
Date: 20140605

ACTIVE INGREDIENTS: HOMOSALATE 0.35 g/3.5 g; OCTINOXATE 0.14 g/3.5 g; AVOBENZONE 0.105 g/3.5 g; OCTOCRYLENE 0.07 g/3.5 g
INACTIVE INGREDIENTS: HIGH DENSITY POLYETHYLENE; CASTOR OIL; CORN OIL; HYDROGENATED POLYBUTENE (1300 MW); DIISOSTEARYL MALATE; ISOSTEARYL HYDROXYSTEARATE; CANDELILLA WAX; TRIISOSTEARYL CITRATE; SILICON DIOXIDE; C12-15 ALKYL LACTATE; TRIMETHYLOLPROPANE TRIISOSTEARATE; TRIDECYL TRIMELLITATE; MEDIUM-CHAIN TRIGLYCERIDES; PHENOXYETHANOL; TOCOPHEROL; D&C RED NO. 7; D&C RED NO. 30; TITANIUM DIOXIDE

LIPSTICK QUEEN ENDLESS SUMMER Broad Spectrum SPF 15 Sunscreen

Drug Facts

ACTIVE INGREDIENT

Active Ingredients Purpose

Homosalate 10% Sunscreen

Octinoxate 4% Sunscreen

Avobenzone 3% Sunscreen

Octocrylene 2% Sunscreen

Uses

- helps prevent sunburn
- if used as directed with other sunburn protection measures (see Directions), decreases the risk of skin cancer and early skin aging caused by the sun

Warnings

For external use only.

Do not use on damaged or broken skin.

When using this product keep out of eyes. Rinse with water to remove.

Stop use and ask a doctor if rash occurs.

Keep out of reach of children. If swallowed, get medical help or contact a Poison Control Center right away.

Directions

- apply liberally 15 minutes before sun exposure
- children under 6 months of age: Ask a doctor
- reapply at least every 2 hours
- use a water-resistant sunscreen if swimming or sweating
- Sun Protection Measures. Spending time in the sun increases your risk of skin cancer and early skin aging. To decrease this risk, regularly use a sunscreen with a broad spectrum SPF of 15 or higher and other sun protection measures including:

- limit time in the sun, especially from 10 a.m. - 2 p.m.

- wear long-sleeve shirts, pants, hats, and sunglasses

Inactive Ingredients (Aloha Shade)

Polyethylene, Ricinus Communis (Castor) Seed Oil, Vegetable Oil (Olus/Huile Vegetale), Hydrogenated Polyisobutene, Diisostearyl Malate, Perfluorononylethyl Stearyl Dimethicone, Isostearyl Hydroxystearate, Euphorbia Cerifera (Candelilla) Wax (Candelilla Cera/Cire De Candelilla), Triisostearyl Citrate, Silica, C12-15 Alkyl Lactate, Trimethylolpropane Triisostearate, Tridecyl Trimellitate, Hydrogenated Vegetable Oil, Caprylic/Capric Triglyceride, Hydrogenated Polycyclopentadiene, Phenoxyethanol, Tocopherol, Red 7 Lake (CI 15850), Red 30 Lake (CI 73360), Titanium Dioxide (CI 77891).

Inactive Ingredients (Hang Ten Shade)

Polyethylene, Vegetable Oil (Olus/Huile Vegetale), Ricinus Communis (Castor) Seed Oil, Hydrogenated Polyisobutene, Diisostearyl Malate, Perfluorononylethyl Stearyl Dimethicone, Isostearyl Hydroxystearate, Euphorbia Cerifera (Candelilla) Wax (Candelilla Cera/Cire De Candelilla), Triisostearyl Citrate, C12-15 Alkyl Lactate, Silica, Trimethylolpropane Triisostearate, Tridecyl Trimellitate, Hydrogenated Vegetable Oil, Caprylic/Capric Triglyceride, Hydrogenated Polycyclopentadiene, Phenoxyethanol, Tocopherol, Red 7 Lake (CI 15850), Red 30 Lake (CI 73360), Iron Oxides (CI 77492, CI 77499), Titanium Dioxide (CI 77891).

Inactive Ingredients (Perfect Wave Shade)

Polyethylene, Ricinus Communis (Castor) Seed Oil, Vegetable Oil (Olus/Huile Vegetale), Hydrogenated Polyisobutene, Diisostearyl Malate, Perfluorononylethyl Stearyl Dimethicone, Isostearyl Hydroxystearate, Euphorbia Cerifera (Candelilla) Wax (Candelilla Cera/Cire De Candelilla), Triisostearyl Citrate, C12-15 Alkyl Lactate, Silica, Trimethylolpropane Triisostearate, Tridecyl Trimellitate, Hydrogenated Vegetable Oil, Caprylic/Capric Triglyceride, Hydrogenated Polycyclopentadiene, Phenoxyethanol, Tocopherol, Red 6 (CI 15850), Yellow 6 Lake (CI 15985), Red 22 (CI 45380), Red 28 Lake (CI 45410), Titanium Dioxide (CI 77891).

Inactive Ingredients (Stoked Shade)

Polyethylene, Vegetable Oil (Olus/Huile Vegetale), Hydrogenated Polyisobutene, Ricinus Communis (Castor) Seed Oil, Diisostearyl Malate, Perfluorononylethyl Stearyl Dimethicone, Isostearyl Hydroxystearate, Euphorbia Cerifera (Candelilla) Wax (Candelilla Cera/Cire De Candelilla), Triisostearyl Citrate, C12-15 Alkyl Lactate, Silica, Trimethylolpropane Triisostearate, Tridecyl Trimellitate, Hydrogenated Vegetable Oil, Caprylic/Capric Triglyceride, Hydrogenated Polycyclopentadiene, Phenoxyethanol, Tocopherol, Red 30 Lake (CI 73360), Iron Oxides (CI 77492), Titanium Dioxide (CI 77891).

Other Information

- protect this product from excessive heat and direct sun